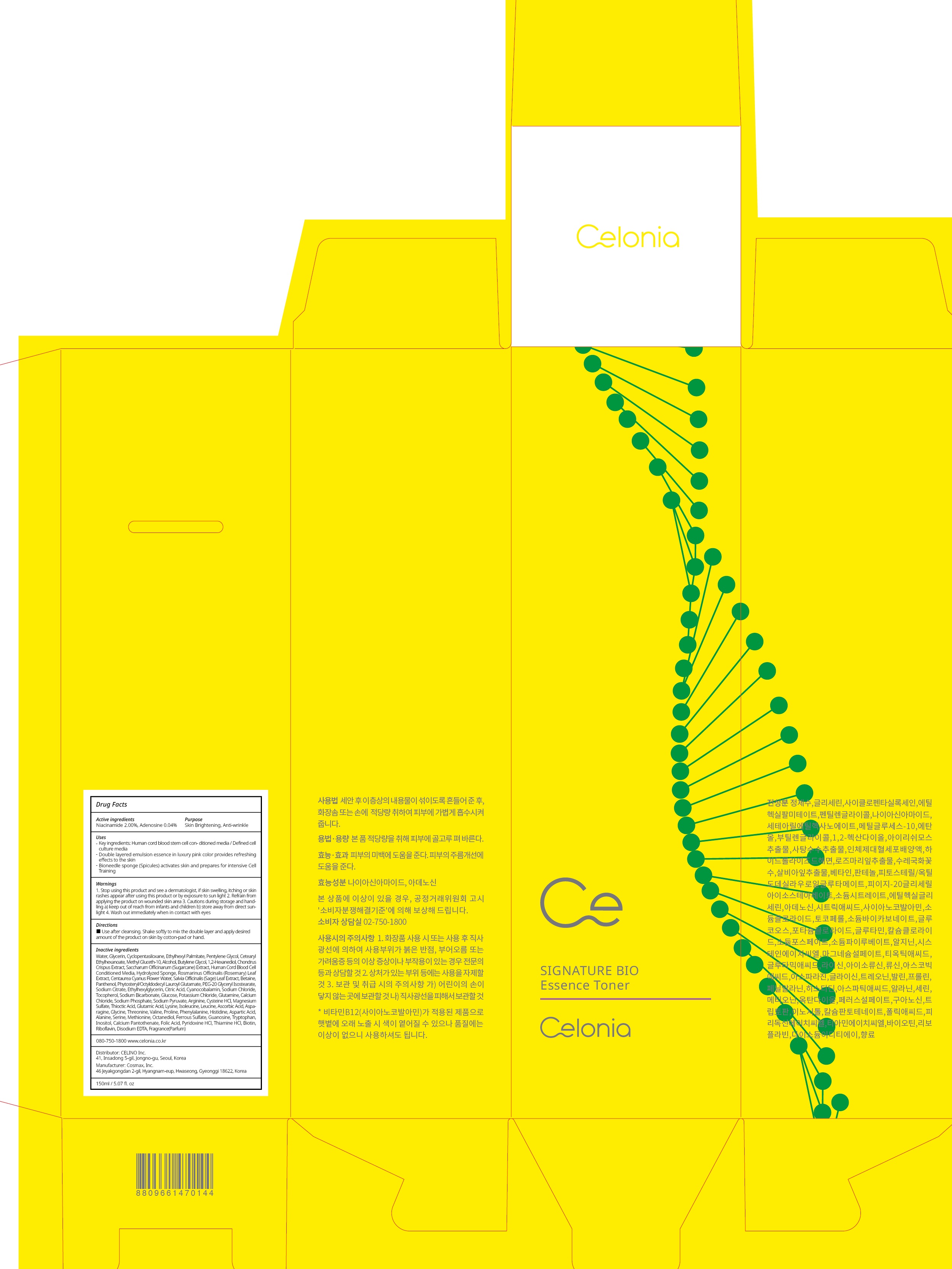 DRUG LABEL: CELONIA SIGNATURE BIO ESSENCE TONER
NDC: 73655-030 | Form: LIQUID
Manufacturer: Celino Inc.
Category: otc | Type: HUMAN OTC DRUG LABEL
Date: 20200310

ACTIVE INGREDIENTS: Niacinamide 3.00 g/150 mL; Adenosine 0.06 g/150 mL
INACTIVE INGREDIENTS: Water; Glycerin

ACTIVE INGREDIENT

Active ingredients: Niacinamide 2.00%, Adenosine 0.04%

INACTIVE INGREDIENT

Inactive ingredients:

Water,Glycerin,Cyclopentasiloxane,Ethylhexyl Palmitate,Pentylene Glycol,
Cetearyl Ethylhexanoate,Methyl Gluceth-10,Alcohol,Butylene Glycol,1,2-Hexanediol,Chondrus Crispus Extract,Saccharum Officinarum (Sugarcane) Extract,Human Cord Blood Cell Conditioned Media,Hydrolyzed Sponge,Rosmarinus Officinalis (Rosemary) Leaf Extract,Centaurea Cyanus Flower Water,Salvia Officinalis (Sage) Leaf Extract,Betaine,Panthenol,Phytosteryl/Octyldodecyl Lauroyl Glutamate,PEG-20 Glyceryl Isostearate,Sodium Citrate,Ethylhexylglycerin, Citric Acid,Cyanocobalamin,Sodium Chloride,Tocopherol,Sodium Bicarbonate,Glucose,Potassium Chloride,Glutamine,Calcium Chloride,Sodium Phosphate,Sodium Pyruvate,Arginine,Cysteine HCl,Magnesium Sulfate,Thioctic Acid,Glutamic Acid,Lysine,Isoleucine,Leucine,Ascorbic Acid,Asparagine,Glycine,Threonine,Valine,Proline,Phenylalanine,Histidine,Aspartic Acid,Alanine,Serine,Methionine,Octanediol,Ferrous Sulfate,Guanosine,Tryptophan,Inositol,Calcium Pantothenate,Folic Acid,Pyridoxine HCl,Thiamine HCl,Biotin,Riboflavin,Disodium EDTA,Fragrance(Parfum)

PURPOSE

Purpose: Skin Brightening, Anti-wrinkle

WARNINGS

1. Stop using this product and see a dermatologist, if skin swelling, itching or skin rashes appear after using this product or by exposure to sun light

2. Refrain from applying the product on wounded skin area

3. Cautions during storage and handling a) keep out of reach from infants and children b) store away from direct sunlight

4. Wash out immediately when in contact with eyes

KEEP OUT OF REACH OF CHILDREN

keep out of reach from infants and children

QUESTIONS

080-750-1800

www.celonia.co.kr

Uses

Key ingredients: Human cord blood stem cell conditioned media / Defined cell culture media
Double layered emulsion essence in luxury pink color provides refreshing effects to the skin
Bioneedle sponge (Spicules) activates skin and prepares for intensive Cell Training

Directions

Use after cleansing. Shake softly to mix the double layer and apply desired amount of the product on skin by cotton-pad or hand.